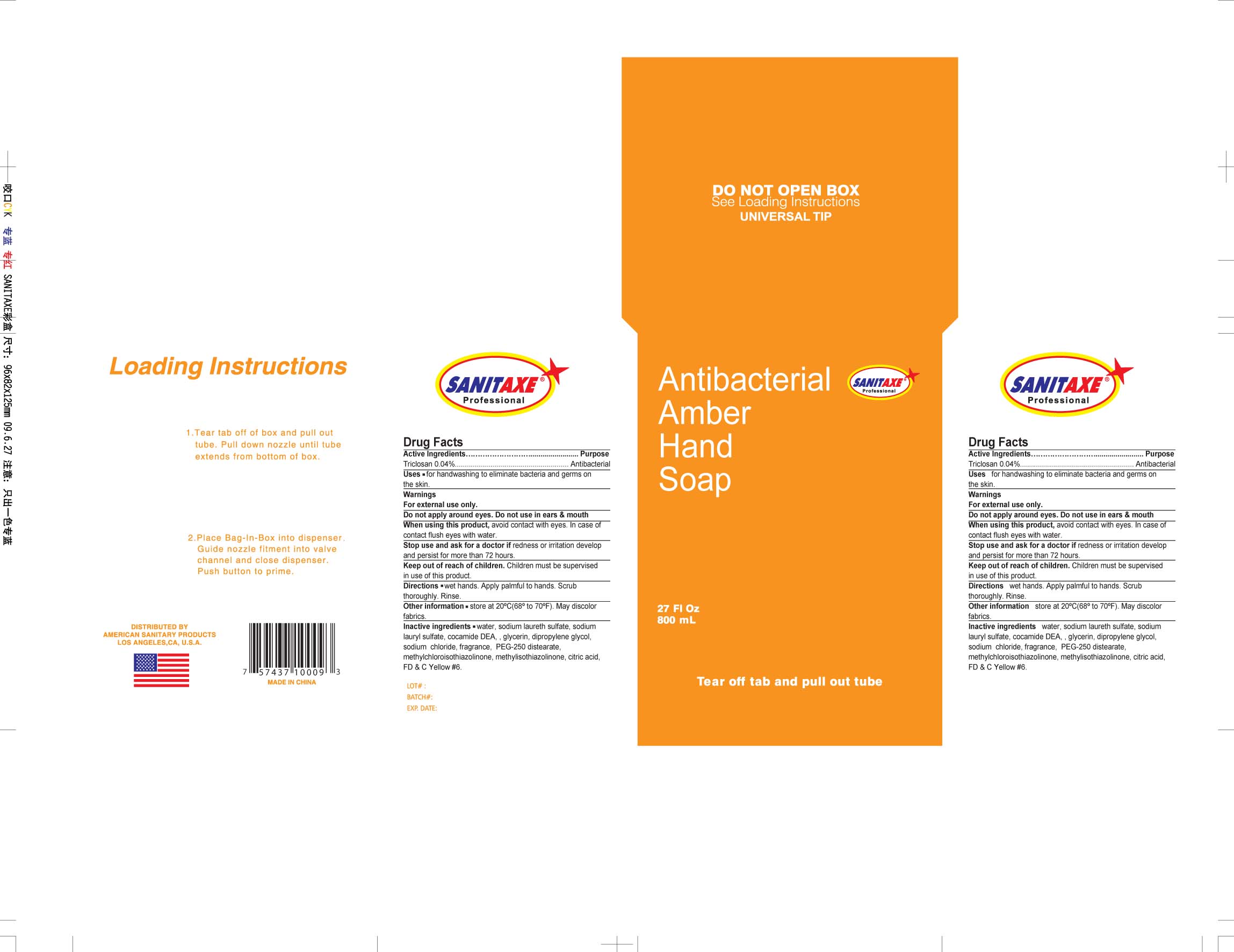 DRUG LABEL: ANTIBACTERIAL AMBER HAND SOAP
NDC: 29860-002 | Form: LIQUID
Manufacturer: Ningbo United Group Import and Export Co. Ltd.
Category: otc | Type: HUMAN OTC DRUG LABEL
Date: 20110315

ACTIVE INGREDIENTS: TRICLOSAN .04 mL/100 mL
INACTIVE INGREDIENTS: WATER 77 mL/100 mL; SODIUM LAURETH SULFATE 12 mL/100 mL; SODIUM LAURYL SULFATE 4 mL/100 mL; GLYCERIN 2 mL/100 mL; SODIUM CHLORIDE .70 mL/100 mL; METHYLISOTHIAZOLINONE .05 mL/100 mL; CITRIC ACID MONOHYDRATE .10 mL/100 mL

Warnings

For external use only

- flammable, keep away from fire and flame
- will produce serious gastric disturbances if taken internally

Ask a doctor before use if you have deep puncture wounds or serious burns

When using this product

- do not get into eyes or mucous membranes
- use only in a well-ventilated area

Stop use and ask a doctor if condition persists or gets worse.

Keep out of reach of children. In case of an accidental ingestion, contact a Poison Control Center immediately.

Drug Facts

Active ingredients

Triclosan 0.04%

Purpose

Antibacterial

Uses

for hand washing to eliminate bacteria and germs on the skin.

Warnings

For external use only.

DO NOT USE

Do not apply around eyes. Do not use in ears and mouth

When using this product, avoid contact with eyes. In case of contact flush eyes with water.

Stop use and ask a doctor if redness or irritation develop and persist for more than 72 hours.

Keep out of reach of children. Children must be supervised in use of this product.

Directions

Wet hands. Apply palmful to hands. Scrub thoroughly. Rinse.

Other information

store at 20C (68F to 70F). May discolor fabrics.

Inactive ingredients

Water, Sodium Laureth Sulfate, Sodium Lauryl Sulfate, Cocamide DEA, Glycerin, Dipropylene Glycol, Sodium Chloride, Fragrance, PEG-250 Distearate, Methylchloroisothiazolinone, Methylisothiazolinone, Citric Acid, FD C Yellow No. 6

PACKAGE LABEL

Enter section text here